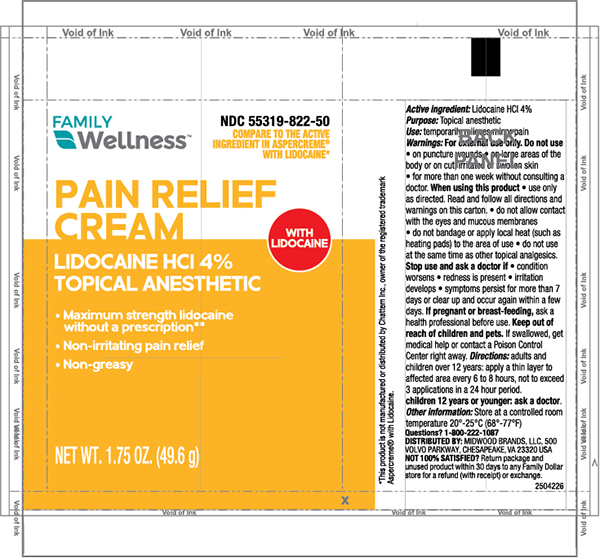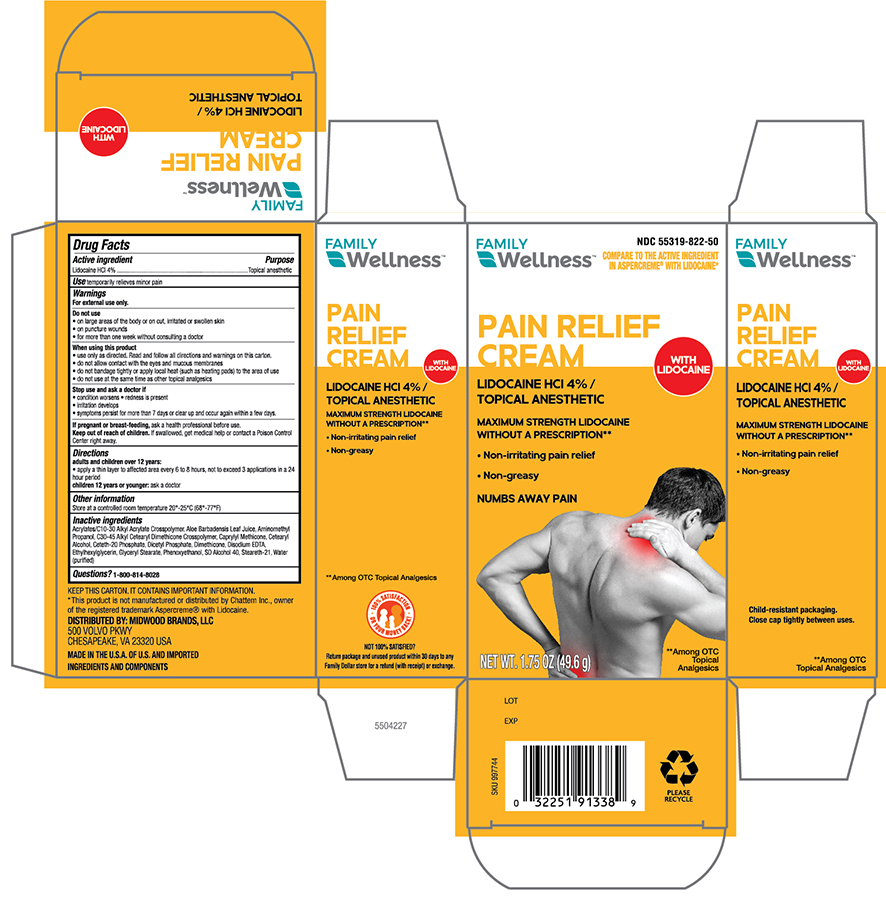 DRUG LABEL: Family Wellness Pain Relief with Lidocaine
NDC: 55319-822 | Form: CREAM
Manufacturer: FAMILY DOLLAR (Family Wellness)
Category: otc | Type: HUMAN OTC DRUG LABEL
Date: 20230829

ACTIVE INGREDIENTS: LIDOCAINE HYDROCHLORIDE 40 mg/1 g
INACTIVE INGREDIENTS: CARBOMER INTERPOLYMER TYPE A (55000 CPS); ALOE VERA LEAF; AMINOMETHYLPROPANOL; C30-45 ALKYL CETEARYL DIMETHICONE CROSSPOLYMER; CAPRYLYL TRISILOXANE; CETOSTEARYL ALCOHOl; CETETH-20 PHOSPHATE; Dihexadecyl phosphate; DIMETHICONE; EDETATE DISODIUM; ETHYLHEXYLGLYCERIN; GLYCERYL STEARATE SE; PHENOXYETHANOL; ALCOHOL; STEARETH-21; WATER

Family Wellness Pain Relief Cream with Lidocaine

Active

Lidocaine HCL 4%

Purpose

Topical anesthetic

Uses

Temporarily relieves minor pain

Warnings

For external use only

Do not use

- on large areas of the body or on cut,irritated or swollen skin
- on puncture wounds
- for more than one week without consulting a doctor

When using this product

- use only as directed. Read and follow all directions and warnings on this carton.
- do not allow contact with the eyes or mucous membranes
- do not bandage or apply local heat (such as heating pads) to the area of use.
- do not use at the same time as other topcial analgesics

Stop use and ask a doctor if

- condition worsens
- symptons persist for more than 7 days or clear up and occur again within a few days.
- If pregnant or breast feeding, ask a health professional before use.
- If pregnant or breast-feeding- ask a health professional before use.

Keep out of reach of children

If swallowed, get medical help or contact Poison Control Center right away.

Directions

- Adults and children over 12 years:
- apply a thin layer to affected area every 6 to 8 hours, not to exceed 3 applications in a 24 hour period
- Children under 12 years or younger: ask a doctor

Other information

Store at controlled room temperature 20°-25°C (68°-77°F)

Inactive Ingredients

Acrylates/C10-30 Alkyl Acrylate Crosspolymer, Aloe Barbadensis Leaf Juice, Aminomethyl Propanol, C30-45 Alkyl Cetearyl Dimethicone Crosspolymer, Caprylyl Methicone, Cetearyl Alcohol, Ceteth-20 Phosphate, Dicetyl Phosphate, Dimethicone, Disodium EDTA, Ethylhexylglycerin, Glyceryl Stearate, Phenoxyethanol, SD Alcohol 40, Steareth-21, Water (purified)

Questions ?

1-800-814-8028

Principal Display panel -Tube

Family Wellness NDC 55319-822-50

Pain Relief Cream

Lidocaine HCL 4%

Topical Anesthetic

NET WT. 1.75 OZ (49.6g)

Principal Display Panel -Carton

Family Wellness NDC 55319-822-50

Pain Relief Cream

Lidocaine HCL 4%

Topical Anesthetic

NET WT. 1.75 OZ (49.6g)